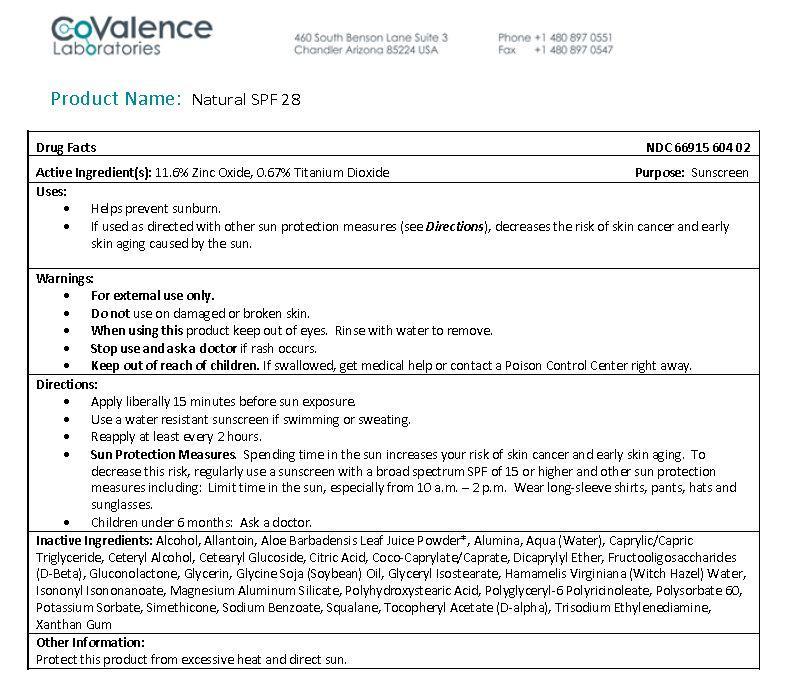 DRUG LABEL: Natural SPF 28
NDC: 66915-604 | Form: CREAM
Manufacturer: CoValence, Inc.
Category: otc | Type: HUMAN OTC DRUG LABEL
Date: 20131202

ACTIVE INGREDIENTS: ZINC OXIDE .116 g/1 g; TITANIUM DIOXIDE .0067 g/1 g
INACTIVE INGREDIENTS: WATER 1 g/1 g; MEDIUM-CHAIN TRIGLYCERIDES 1 g/1 g; CETOSTEARYL ALCOHOL 1 g/1 g; CETEARYL GLUCOSIDE 1 g/1 g; COCO-CAPRYLATE/CAPRATE 1 g/1 g; POLYSORBATE 60 1 g/1 g; GLYCERIN 1 g/1 g; SQUALANE 1 g/1 g; POLYGLYCERYL-6 DIOLEATE 1 g/1 g; ISONONYL ISONONANOATE 1 g/1 g; MAGNESIUM ALUMINUM SILICATE 1 g/1 g; XANTHAN GUM 1 g/1 g; GLYCERYL ISOSTEARATE 1 g/1 g; POLYHYDROXYSTEARIC ACID (2300 MW) 1 g/1 g; ALUMINUM OXIDE 1 g/1 g; .ALPHA.-TOCOPHEROL ACETATE, D- 1 g/1 g; SOYBEAN OIL 1 g/1 g; ALOE VERA LEAF 1 g/1 g; DIMETHICONE 1 g/1 g; ALLANTOIN 1 g/1 g; POTASSIUM SORBATE 1 g/1 g; TRISODIUM ETHYLENEDIAMINE DISUCCINATE 1 g/1 g; CITRIC ACID MONOHYDRATE 1 g/1 g; POPULUS TREMULOIDES BARK 1 g/1 g; DICAPRYLYL ETHER 1 g/1 g; 1,2-HEXANEDIOL 1 g/1 g; CAPRYLYL GLYCOL 1 g/1 g; GLUCONOLACTONE 1 g/1 g; LONICERA CAPRIFOLIUM FLOWER 1 g/1 g; LONICERA JAPONICA FLOWER 1 g/1 g; TROPOLONE 1 g/1 g

Drug Facts

Active Ingredient(s):

11.6% Zinc Oxide, 0.67% Titanium Dioxide

Purpose:

Sunscreen

Warnings: (Keep Out Of Reach Of Children)

- Keep out of reach of children. If swallowed, get medical help or contact a Poison Control Center right away.

Uses:

- Helps prevent sunburn.
- If used as directed with other sun protection measures (see Directions), decreases the risk of skin cancer and early skin aging caused by the sun.

Warnings:

- For external use only.
- Do not use on damaged or broken skin.
- When using this product keep out of eyes. Rinse with water to remove.
- Stop use and ask a doctor if a rash occurs.

Directions:

- Apply liberally 15 minutes before sun exposure.
- Use a water resistant sunscreen if swimming or sweating.
- Reapply at least every 2 hours.
- Sun Protection Measures. Spending time in the sun increases your risk of skin cancer and early skin aging. To decrease this risk, regularly use a sunscreen with a broad spectrum SPF of 15 or higher and other sun protection measures including: Limit time in the sun, especially from 10 a.m. - 2 p.m. Wear long-sleeve shirts, pants, hats and sunglasses.
- Children under 6 months: Ask a doctor.

Inactive Ingredients:

Alcohol, Allantoin, Aloe Barbadensis Leaf Juice Powder, Alumina, Aqua (Water), Caprylic/Capric Triglyceride, Ceteryl Alcohol, Cetearyl Glucoside, Citric Acid, Coco-Caprylate/Caprate, Dicaprylyl Ether, Fructooligosaccharides (D-Beta), Gluconolactone, Glycerin, Glycine Soja (Soybean) Oil, Glyceryl Isostearate, Hamamelis Virginiana (Witch Hazel) Water, Isononyl Isononanoate, Magnesium Aluminum Silicate, Polyhydroxystearic Acid, Polyglyceryl-6 Polyricinoleate, Polysorbate 60, Potassium Sorbate, Simethicone, Sodium Benzoate, Squalane, Tocopheryl Acetate (D-alpha), Trisodium Ethylenediamine, Xanthan Gum

Other Information:

Protect this product from excessive heat and direct sun.